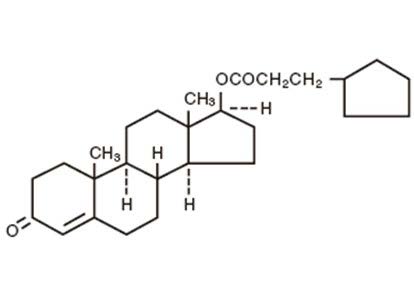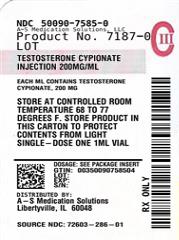 DRUG LABEL: testosterone cypionate
NDC: 50090-7585 | Form: INJECTION, SOLUTION
Manufacturer: A-S Medication Solutions
Category: prescription | Type: HUMAN PRESCRIPTION DRUG LABEL
Date: 20260124
DEA Schedule: CIII

ACTIVE INGREDIENTS: TESTOSTERONE CYPIONATE 200 mg/1 mL
INACTIVE INGREDIENTS: BENZYL BENZOATE 0.2 mL/1 mL; COTTONSEED OIL 556.24 mg/1 mL; BENZYL ALCOHOL 9.45 mg/1 mL

Testosterone Cypionate Injection, USP CIII

DESCRIPTION

Testosterone Cypionate Injection, USP, for intramuscular injection, contains testosterone cypionate which is the oil-soluble 17 (beta)- cyclopentylpropionate ester of the androgenic hormone testosterone.

Testosterone cypionate is a white or creamy white crystalline powder, odorless or nearly so and stable in air. It is insoluble in water, freely soluble in alcohol, chloroform, dioxane, ether, and soluble in vegetable oils.

The chemical name for testosterone cypionate is androst-4-en-3-one, 17-(3-cyclopentyl-1-oxopropoxy)-, (17β)-. Its molecular formula is C27H40O3, and the molecular weight 412.61.

The structural formula is represented below:

Testosterone Cypionate Injection, USP is available in two strengths, 100 mg/mL and 200 mg/mL testosterone cypionate.

Each mL of the 100 mg/mLsolution contains:
Testosterone cypionate | 100 mg
Benzyl benzoate | 0.1 mL
Cottonseed oil | 732.79 mg
Benzyl alcohol (as preservative) | 9.45 mg
Each mL of the 200 mg/mLsolution contains:
Testosterone cypionate | 200 mg
Benzyl benzoate | 0.2 mL
Cottonseed oil | 556.24 mg
Benzyl alcohol (as preservative) | 9.45 mg

CLINICAL PHARMACOLOGY

Endogenous androgens are responsible for normal growth and development of the male sex organs and for maintenance of secondary sex characteristics. These effects include growth and maturation of the prostate, seminal vesicles, penis, and scrotum; development of male hair distribution, such as beard, pubic, chest, and axillary hair; laryngeal enlargement, vocal cord thickening, and alterations in body musculature and fat distribution. Drugs in this class also cause retention of nitrogen, sodium, potassium, and phosphorous, and decreased urinary excretion of calcium. Androgens have been reported to increase protein anabolism and decrease protein catabolism. Nitrogen balance is improved only when there is sufficient intake of calories and protein.

Androgens are responsible for the growth spurt of adolescence and for eventual termination of linear growth, brought about by fusion of the epiphyseal growth centers. In children, exogenous androgens accelerate linear growth rates, but may cause disproportionate advancement in bone maturation. Use over long periods may result in fusion of the epiphyseal growth centers and termination of the growth process. Androgens have been reported to stimulate production of red blood cells by enhancing production of erythropoietic stimulation factor.

During exogenous administration of androgens, endogenous testosterone release is inhibited through feedback inhibition of pituitary luteinizing hormone (LH). At large doses of exogenous androgens, spermatogenesis may also be suppressed through feedback inhibition of pituitary follicle stimulating hormone (FSH).

There is a lack of substantial evidence that androgens are effective in fractures, surgery, convalescence, and functional uterine bleeding.

Pharmacokinetics

Testosterone esters are less polar than free testosterone. Testosterone esters in oil injected intramuscularly are absorbed slowly from the lipid phase; thus, testosterone cypionate can be given at intervals of two to four weeks.

Testosterone in plasma is 98 percent bound to a specific testosterone-estradiol binding globulin, and about 2 percent is free. Generally, the amount of this sex-hormone binding globulin in the plasma will determine the distribution of testosterone between free and bound forms, and the free testosterone concentration will determine its half-life.

About 90 percent of a dose of testosterone is excreted in the urine as glucuronic and sulfuric acid conjugates of testosterone and its metabolites; about 6 percent of a dose is excreted in the feces, mostly in the unconjugated form. Inactivation of testosterone occurs primarily in the liver. Testosterone is metabolized to various 17-keto steroids through two different pathways.

The half-life of testosterone cypionate when injected intramuscularly is approximately eight days.

In many tissues the activity of testosterone appears to depend on reduction to dihydrotestosterone, which binds to cytosol receptor proteins. The steroid-receptor complex is transported to the nucleus where it initiates transcription events and cellular changes related to androgen action.

INDICATIONS AND USAGE

Testosterone Cypionate Injection is indicated for replacement therapy in the male in conditions associated with symptoms of deficiency or absence of endogenous testosterone.

1. Primary hypogonadism (congenital or acquired)-testicular failure due to cryptorchidism, bilateral torsion, orchitis, vanishing testis syndrome; or orchidectomy.

2. Hypogonadotropic hypogonadism (congenital or acquired) - gonadotropin or LHRH deficiency, or pituitary-hypothalamic injury from tumors, trauma, or radiation.

Safety and efficacy of Testosterone Cypionate Injection in men with "age-related hypogonadism" (also referred to as "late-onset hypogonadism") have not been established.

CONTRAINDICATIONS

1. Known hypersensitivity to the drug
2. Males with carcinoma of the breast
3. Males with known or suspected carcinoma of the prostate gland
4. Women who are pregnant (see PRECAUTIONS, Pregnancy)
5. Patients with serious cardiac, hepatic or renal disease (see WARNINGS)

WARNINGS

Hypercalcemia may occur in immobilized patients. If this occurs, the drug should be discontinued.

Prolonged use of high doses of androgens (principally the 17-α alkyl-androgens) has been associated with development of hepatic adenomas, hepatocellular carcinoma, and peliosis hepatis —all potentially life-threatening complications.

Geriatric patients treated with androgens may be at an increased risk of developing prostatic hypertrophy and prostatic carcinoma although conclusive evidence to support this concept is lacking.

There have been postmarketing reports of venous thromboembolic events, including deep vein thrombosis (DVT) and pulmonary embolism (PE), in patients using testosterone products, such as testosterone cypionate. Evaluate patients who report symptoms of pain, edema, warmth and erythema in the lower extremity for DVT and those who present with acute shortness of breath for PE. If a venous thromboembolic event is suspected, discontinue treatment with testosterone cypionate and initiate appropriate workup and management.

Long term clinical safety trials have not been conducted to assess the cardiovascular outcomes of testosterone replacement therapy in men. To date, epidemiologic studies and randomized controlled trials have been inconclusive for determining the risk of major adverse cardiovascular events (MACE), such as non-fatal myocardial infarction, non-fatal stroke, and cardiovascular death, with the use of testosterone compared to non-use. Some studies, but not all, have reported an increased risk of MACE in association with use of testosterone replacement therapy in men. Patients should be informed of this possible risk when deciding whether to use or to continue to use Testosterone Cypionate Injection.

Testosterone can increase blood pressure which can increase cardiovascular (CV) risk over time. Monitor blood pressure periodically in men using testosterone products, especially in men with hypertension. Testosterone products are not recommended for use in patients with uncontrolled hypertension.

Testosterone has been subject to abuse, typically at doses higher than recommended for the approved indication and in combination with other anabolic androgenic steroids. Anabolic androgenic steroid abuse can lead to serious cardiovascular and psychiatric adverse reactions (see DRUG ABUSE AND DEPENDENCE).

If testosterone abuse is suspected, check serum testosterone concentrations to ensure they are within therapeutic range. However, testosterone levels may be in the normal or subnormal range in men abusing synthetic testosterone derivatives. Counsel patients concerning the serious adverse reactions associated with abuse of testosterone and anabolic androgenic steroids. Conversely, consider the possibility of testosterone and anabolic androgenic steroid abuse in suspected patients who present with serious cardiovascular or psychiatric adverse events.

Edema, with or without congestive heart failure, may be a serious complication in patients with pre-existing cardiac, renal or hepatic disease.

Gynecomastia may develop and occasionally persists in patients being treated for hypogonadism.

The preservative benzyl alcohol has been associated with serious adverse events, including the "gasping syndrome", and death in pediatric patients. Although normal therapeutic doses of this product ordinarily deliver amounts of benzyl alcohol that are substantially lower than those reported in association with the "gasping syndrome", the minimum amount of benzyl alcohol at which toxicity may occur is not known. The risk of benzyl alcohol toxicity depends on the quantity administered and the liver and kidneys' capacity to detoxify the chemical. Premature and low-birth weight infants may be more likely to develop toxicity.

Androgen therapy should be used cautiously in healthy males with delayed puberty. The effect on bone maturation should be monitored by assessing bone age of the wrist and hand every 6 months. In children, androgen treatment may accelerate bone maturation without producing compensatory gain in linear growth. This adverse effect may result in compromised adult stature. The younger the child the greater the risk of compromising final mature height.

This drug has not been shown to be safe and effective for the enhancement of athletic performance. Because of the potential risk of serious adverse health effects, this drug should not be used for such purpose.

PRECAUTIONS

General

Patients with benign prostatic hypertrophy may develop acute urethral obstruction. Priapism or excessive sexual stimulation may develop. Oligospermia may occur after prolonged administration or excessive dosage. If any of these effects appear, the androgen should be stopped and if restarted, a lower dosage should be utilized.

Testosterone cypionate should not be used interchangeably with testosterone propionate because of differences in duration of action.

Testosterone cypionate is notfor intravenous use.

Information for patients

Patients should be instructed to report any of the following: nausea, vomiting, changes in skin color, ankle swelling, too frequent or persistent erections of the penis.

Laboratory tests

Hemoglobin and hematocrit levels (to detect polycythemia) should be checked periodically in patients receiving long-term androgen administration.

Serum cholesterol may increase during androgen therapy.

Drug interactions

Androgens may increase sensitivity to oral anticoagulants. Dosage of the anticoagulant may require reduction in order to maintain satisfactory therapeutic hypoprothrombinemia.

Concurrent administration of oxyphenbutazone and androgens may result in elevated serum levels of oxyphenbutazone.

In diabetic patients, the metabolic effects of androgens may decrease blood glucose and, therefore, insulin requirements.

Drug/Laboratory test Interferences

Androgens may decrease levels of thyroxine-binding globulin, resulting in decreased total T4serum levels and increased resin uptake of T3and T4. Free thyroid hormone levels remain unchanged, however, and there is no clinical evidence of thyroid dysfunction.

Carcinogenesis

Animal data

Testosterone has been tested by subcutaneous injection and implantation in mice and rats. The implant induced cervical-uterine tumors in mice, which metastasized in some cases. There is suggestive evidence that injection of testosterone into some strains of female mice increases their susceptibility to hepatoma. Testosterone is also known to increase the number of tumors and decrease the degree of differentiation of chemically induced carcinomas of the liver in rats.

Human data

There are rare reports of hepatocellular carcinoma in patients receiving long-term therapy with androgens in high doses. Withdrawal of the drugs did not lead to regression of the tumors in all cases.

Geriatric patients treated with androgens may be at an increased risk of developing prostatic hypertrophy and prostatic carcinoma although conclusive evidence to support this concept is lacking.

Pregnancy

Teratogenic Effects

The use of testosterone in women who are pregnant is contraindicated. Testosterone is teratogenic and may cause fetal harm. Testosterone is known to cause virilization of the female fetus when administrated to pregnant women.

Benzyl alcohol can cross the placenta. See WARNINGS.

Nursing mothers

Testosterone Cypionate Injection is not recommended for use in nursing mothers.

Pediatric use

Safety and effectiveness in pediatric patients below the age of 12 years have not been established.

ADVERSE REACTIONS

The following adverse reactions in the male have occurred with some androgens:

Endocrine and urogenital: Gynecomastia and excessive frequency and duration of penile erections. Oligospermia may occur at high dosages.

Skin and appendages: Hirsutism, male pattern of baldness, seborrhea, and acne.

Cardiovascular Disorders: myocardial infarction, stroke.

Fluid and electrolyte disturbances: Retention of sodium, chloride, water, potassium, calcium, and inorganic phosphates.

Gastrointestinal: Nausea, cholestatic jaundice, alterations in liver function tests, rarely hepatocellular neoplasms and peliosis hepatis (see WARNINGS).

Hematologic: Suppression of clotting factors II, V, VII, and X, bleeding in patients on concomitant anticoagulant therapy, and polycythemia.

Nervous system: Increased or decreased libido, headache, anxiety, depression, and generalized paresthesia.

Allergic: Hypersensitivity, including skin manifestations and anaphylactoid reactions.

Vascular disorders: Venous thromboembolism.

Special senses: Rare cases of central serous chorioretinopathy (CSCR).

Miscellaneous: Inflammation and pain at the site of intramuscular injection.

DRUG ABUSE AND DEPENDENCE

Controlled Substance

Testosterone Cypionate Injection contains testosterone, a Schedule III controlled substance in the Controlled Substances Act.

Abuse

Drug abuse is intentional non-therapeutic use of a drug, even once, for its rewarding psychological and physiological effects. Abuse and misuse of testosterone are seen in male and female adults and adolescents. Testosterone, often in combination with other anabolic androgenic steroids (AAS), and not obtained by prescription through a pharmacy, may be abused by athletes and bodybuilders. There have been reports of misuse by men taking higher doses of legally obtained testosterone than prescribed and continuing testosterone despite adverse events or against medical advice.

Abuse-Related Adverse Reactions

Serious adverse reactions have been reported in individuals who abuse anabolic androgenic steroids and include cardiac arrest, myocardial infarction, hypertrophic cardiomyopathy, congestive heart failure, cerebrovascular accident, hepatotoxicity, and serious psychiatric manifestations, including major depression, mania, paranoia, psychosis, delusions, hallucinations, hostility and aggression.

The following adverse reactions have also been reported in men: transient ischemic attacks, convulsions, hypomania, irritability, dyslipidemias, testicular atrophy, subfertility, and infertility.

The following additional adverse reactions have been reported in women: hirsutism, virilization, deepening of voice, clitoral enlargement, breast atrophy, male-pattern baldness, and menstrual irregularities.

The following adverse reactions have been reported in male and female adolescents: premature closure of bony epiphyses with termination of growth, and precocious puberty.

Because these reactions are reported voluntarily from a population of uncertain size and may include abuse of other agents, it is not always possible to reliably estimate their frequency or establish a causal relationship to drug exposure.

Dependence

Behaviors Associated with Addiction

Continued abuse of testosterone and other anabolic steroids, leading to addiction is characterized by the following behaviors:

- Taking greater dosages than prescribed
- Continued drug use despite medical and social problems due to drug use
- Spending significant time to obtain the drug when supplies of the drug are interrupted
- Giving a higher priority to drug use than other obligations
- Having difficulty in discontinuing the drug despite desires and attempts to do so
- Experiencing withdrawal symptoms upon abrupt discontinuation of use

Physical dependence is characterized by withdrawal symptoms after abrupt drug discontinuation or a significant dose reduction of a drug. Individuals taking supratherapeutic doses of testosterone may experience withdrawal symptoms lasting for weeks or months which include depressed mood, major depression, fatigue, craving, restlessness, irritability, anorexia, insomnia, decreased libido and hypogonadotropic hypogonadism.

Drug dependence in individuals using approved doses of testosterone for approved indications has not been documented.

OVERDOSAGE

There have been no reports of acute overdosage with the androgens.

DOSAGE AND ADMINISTRATION

Prior to initiating Testosterone Cypionate Injection, USP, confirm the diagnosis of hypogonadism by ensuring that serum testosterone concentrations have been measured in the morning on at least two separate days and that these serum testosterone concentrations are below the normal range.

Testosterone Cypionate Injection, USP is for intramuscular use only.

It should not be given intravenously. Intramuscular injections should be given deep in the gluteal muscle.

The suggested dosage for Testosterone Cypionate Injection, USP varies depending on the age, sex, and diagnosis of the individual patient. Dosage is adjusted according to the patient's response and the appearance of adverse reactions.

Various dosage regimens have been used to induce pubertal changes in hypogonadal males; some experts have advocated lower dosages initially, gradually increasing the dose as puberty progresses, with or without a decrease to maintenance levels. Other experts emphasize that higher dosages are needed to induce pubertal changes and lower dosages can be used for maintenance after puberty. The chronological and skeletal ages must be taken into consideration, both in determining the initial dose and in adjusting the dose.

For replacement in the hypogonadal male, 50 –400 mg should be administered every two to four weeks.

Parenteral drug products should be inspected visually for particulate matter and discoloration prior to administration, whenever solution and container permit. Warming and shaking the vial should redissolve any crystals that may have formed during storage at temperatures lower than recommended.

HOW SUPPLIED

Product: 50090-7585

NDC: 50090-7585-0 1 mL in a VIAL, SINGLE-DOSE / 1 in a CARTON

To report SUSPECTED ADVERSE REACTIONS, contact Northstar @ 1-800-206-7821 or the FDA at 1-800-FDA-1088 or www.fda.gov/medwatch.

Manufactured for:
Northstar Rx LLC, Memphis, TN 38141

Manufactured by:
Laboratorios Farmalan SA 24193

Revised: 07/2025
NOR-PI286-01